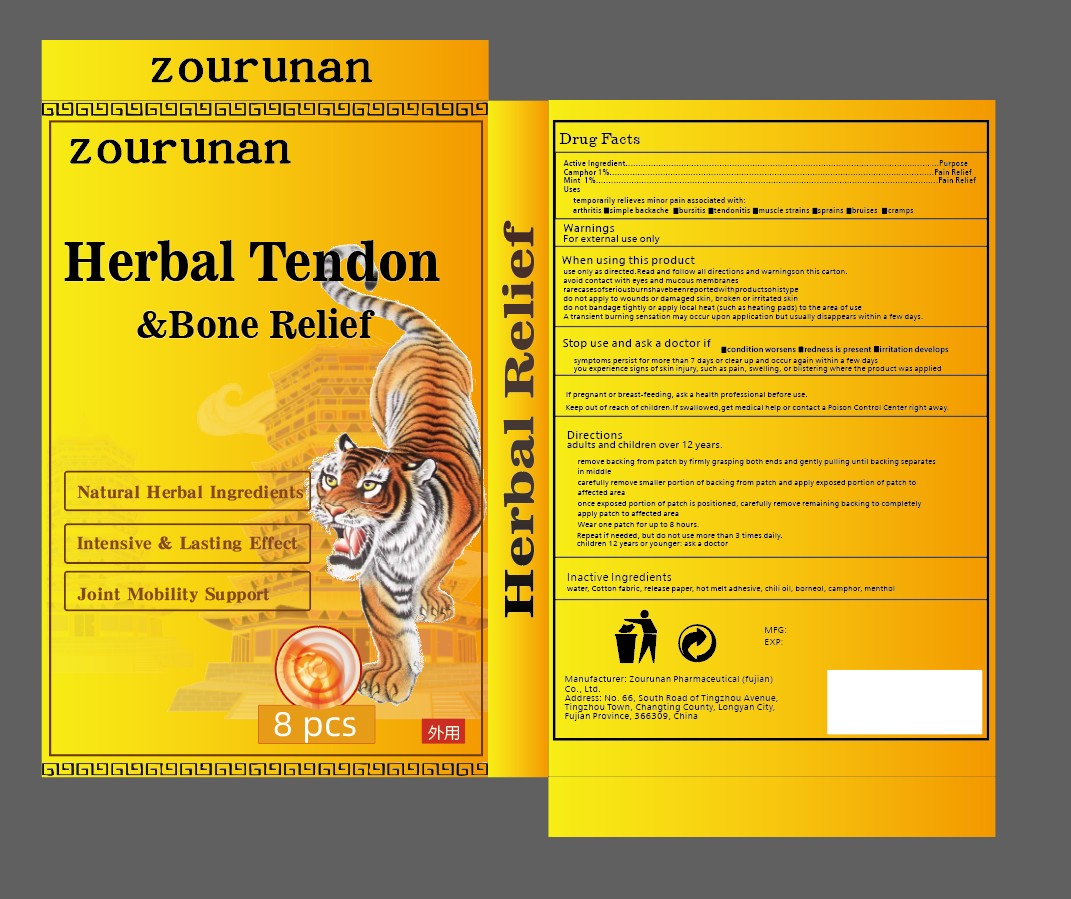 DRUG LABEL: Herbal Tendon Bone Relief
NDC: 87083-010 | Form: PATCH
Manufacturer: Guchutang Biotechnology (Longyan) Co., Ltd.
Category: otc | Type: HUMAN OTC DRUG LABEL
Date: 20251213

ACTIVE INGREDIENTS: MINT 1 g/100 g; CAMPHOR, (-)- 1 g/100 g
INACTIVE INGREDIENTS: MENTHOL; POWDERED CELLULOSE; BORNEOL; COTTON FIBER; CAPSICUM OLEORESIN; WATER

Active ingredient.
camphor
Mint

PURPOSE

emporarily relieves minor pain associated with:
arthritis cimpie backache bursitis tendonitis muscle streins epreins bruises cramps

Keep out of reach of children. If swallowed, get medical help or contact a Poison Control Center immediately

WARNINGS

For external use only.

DOSAGE AND ADMINISTRATION

should be used to 8 hours
ashould be used no more than 3 times a day

INACTIVE INGREDIENT

Water cotton , paper

hotmelt adhesive, chili oil, borneol camphor menthol

INDICATIONS AND USAGE

Adult and children 12 years of age and older:

peel off protective backing and apply sticky side to affected area
carefully remove backing from patch
should be used to 8 hours
ashould be used no more than 3 times a day
Children under 12 years of age: consult a doctor